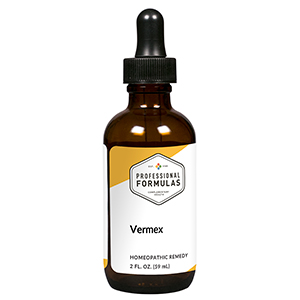 DRUG LABEL: Vermex
NDC: 63083-6016 | Form: LIQUID
Manufacturer: Professional Complementary Health Formulas
Category: homeopathic | Type: HUMAN OTC DRUG LABEL
Date: 20190815

ACTIVE INGREDIENTS: ARTEMISIA CINA PRE-FLOWERING TOP 2 [hp_X]/59 mL; BLACK WALNUT 2 [hp_X]/59 mL; BERBERIS VULGARIS ROOT BARK 3 [hp_X]/59 mL; SPIGELIA MARILANDICA ROOT 3 [hp_X]/59 mL; TEUCRIUM MARUM WHOLE 3 [hp_X]/59 mL; DRYOPTERIS FILIX-MAS ROOT 4 [hp_X]/59 mL; SCHOENOCAULON OFFICINALE SEED 4 [hp_X]/59 mL; WORMWOOD 6 [hp_X]/59 mL; COPPER 6 [hp_X]/59 mL; CLOVE 12 [hp_X]/59 mL
INACTIVE INGREDIENTS: ALCOHOL; WATER

X16

ACTIVE INGREDIENTS

Cina 2X
Juglans nigra 2X
Berberis vulgaris 3X
Spigelia marilandica 3X
Teucrium marum 3X
Filix mas 4X
Sabadilla 4X
Artemisia absinthium 6X
Cuprum metallicum 6X
Eugenia caryophyllata 12X

QUESTIONS

Professional Formulas

PO Box 2034 Lake Oswego, OR 97035

INDICATIONS

For the temporary relief of mild abdominal pain or cramping, bloating, flatulence, constipation or diarrhea, vomiting, or sensation of itchy or crawling skin.*

PURPOSE

*Claims based on traditional homeopathic practice, not accepted medical evidence. Not FDA evaluated.

WARNINGS

Consult a doctor if condition worsens or symptoms persist. Keep out of the reach of children. In case of overdose, get medical help or contact a poison control center right away. If pregnant or breastfeeding, ask a healthcare professional before use.

Keep out of the reach of children.

PREGNANCY OR BREAST FEEDING

If pregnant or breastfeeding, ask a healthcare professional before use.

DIRECTIONS

Place drops under tongue 30 minutes before/after meals. Adults and children 12 years and over: Take 10 drops up to 3 times per day. Consult a physician for use in children under 12 years of age.

OTHER INFORMATION

Tamper resistant. If seal is broken, do not use. After opening, close container tightly and store at room temperature away from heat.

INACTIVE INGREDIENTS

20% ethanol, purified water.

LABEL

Est 1985

Professional Formulas

Complementary Health

Vermex

Homeopathic Remedy

2 FL. OZ. (59 mL)